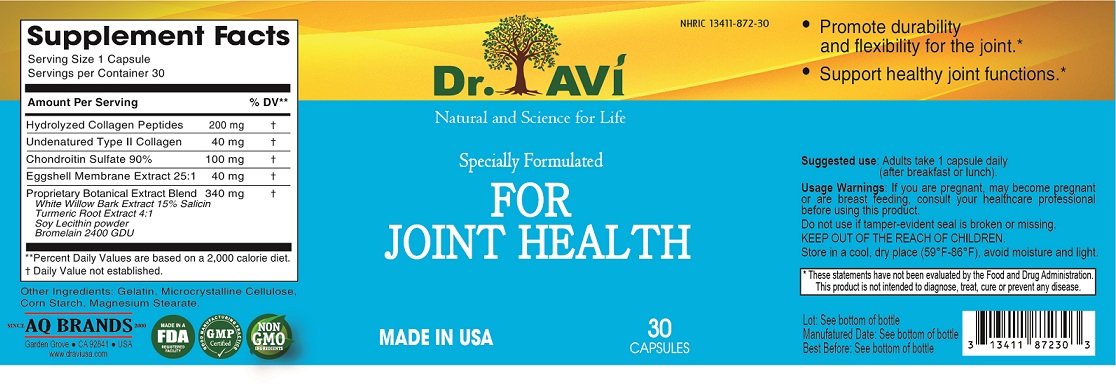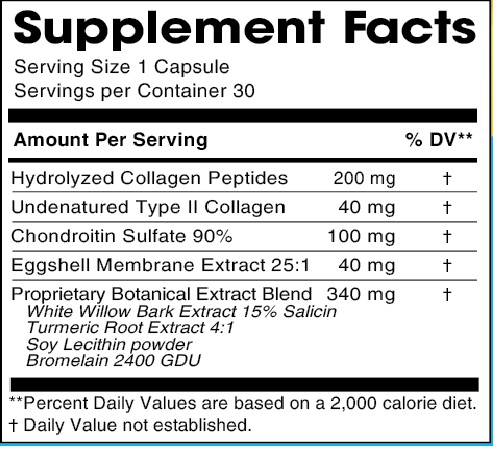 DRUG LABEL: Dr. Avi For Joint Health
NDC: 13411-872 | Form: CAPSULE
Manufacturer: Advanced Pharmaceutical Services, Inc. Dba Affordable Quality Pharmaceuticals
Category: other | Type: DIETARY SUPPLEMENT
Date: 20210412

ACTIVE INGREDIENTS: HYDROLYSED BOVINE COLLAGEN (ENZYMATIC; 3500 MW) 200 mg/1 1; CHICKEN CARTILAGE 40 mg/1 1; CHONDROITIN SULFATE (BOVINE) 100 mg/1 1; EGG SHELL MEMBRANE 40 mg/1 1; SALIX ALBA BARK 250 mg/1 1; TURMERIC 60 mg/1 1; LECITHIN, SOYBEAN 20 mg/1 1; STEM BROMELAIN 10 mg/1 1
INACTIVE INGREDIENTS: GELATIN, UNSPECIFIED; MICROCRYSTALLINE CELLULOSE; STARCH, CORN; MAGNESIUM STEARATE

Identity

DIETARY SUPPLEMENT

Warning

If you are pregnant, may become pregnant or are breast feeding, consult your healthcare professional before using this product.

Safe handling and warning

Do not use if tamper-evident seal is broken or missing.

Store in a cool, dry place (59°F-86°F), avoid moisture and light.

Health claim

• Promote durability and flexibility for the joint*.
• Support healthy joint functions*.

* These statements have not been evaluated by the Food & Drug Administration. This product is not intended to diagnose, treat, cure, or prevent any disease.

Direction

Adults take 1 capsule daily (after breakfast or lunch).